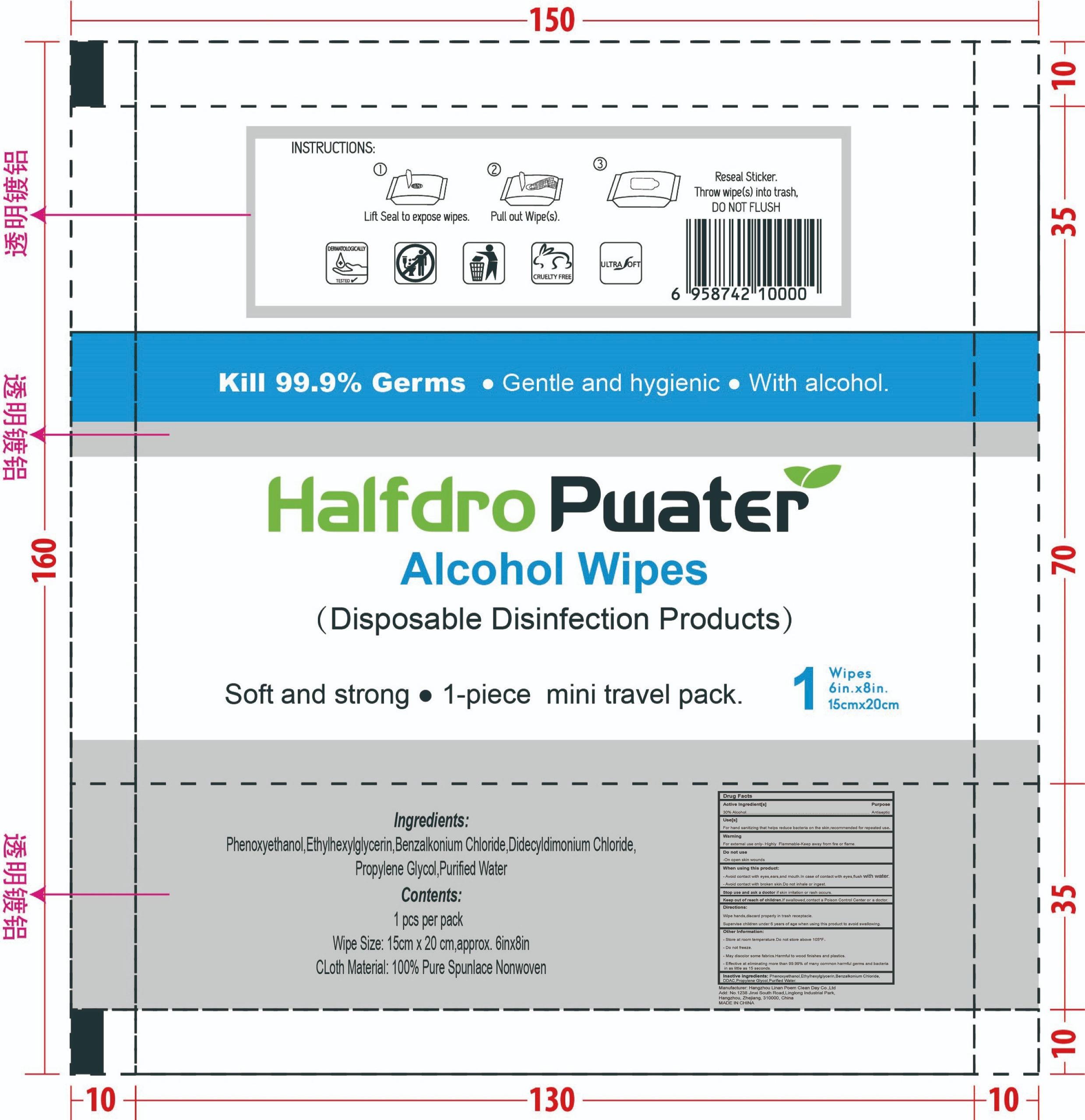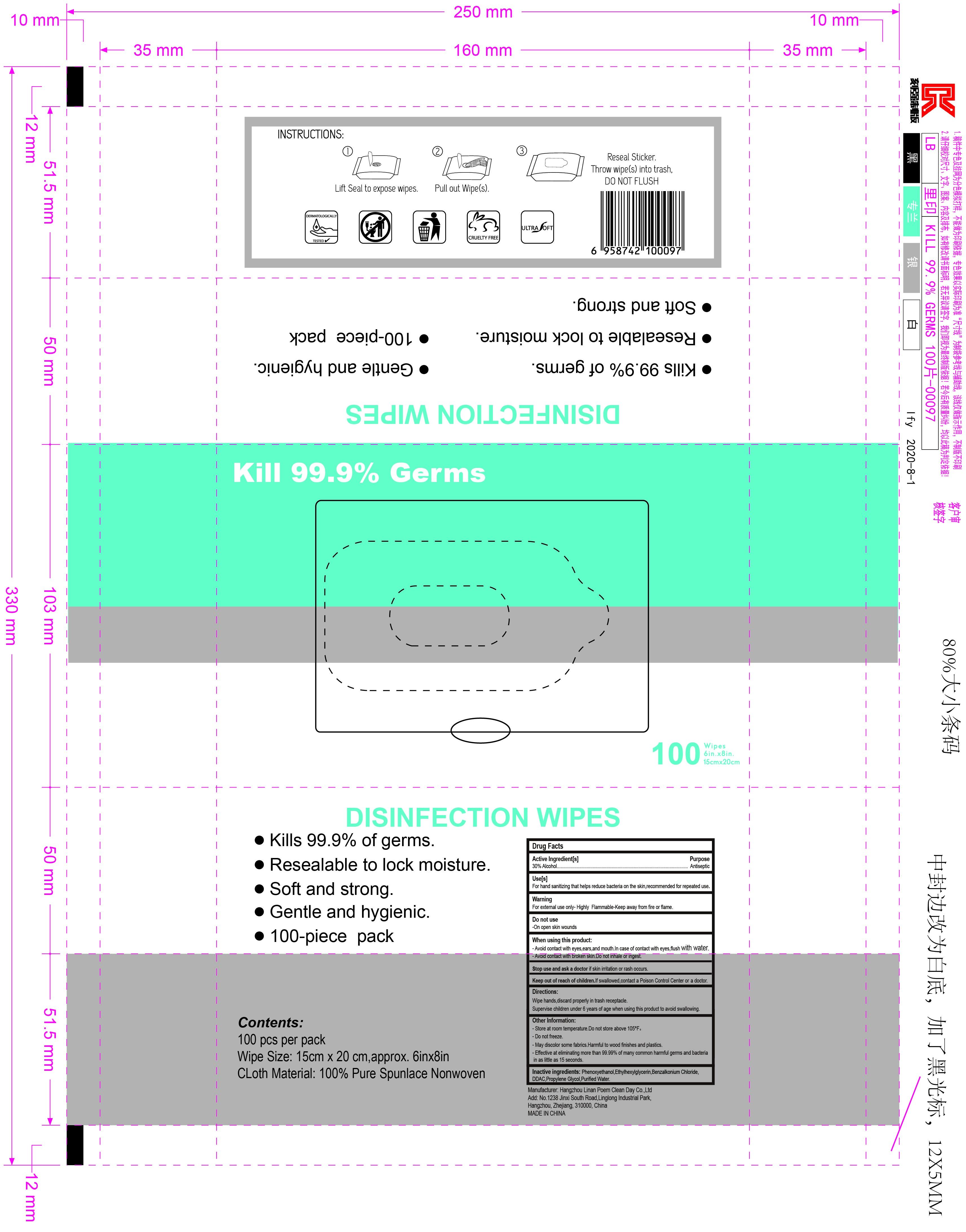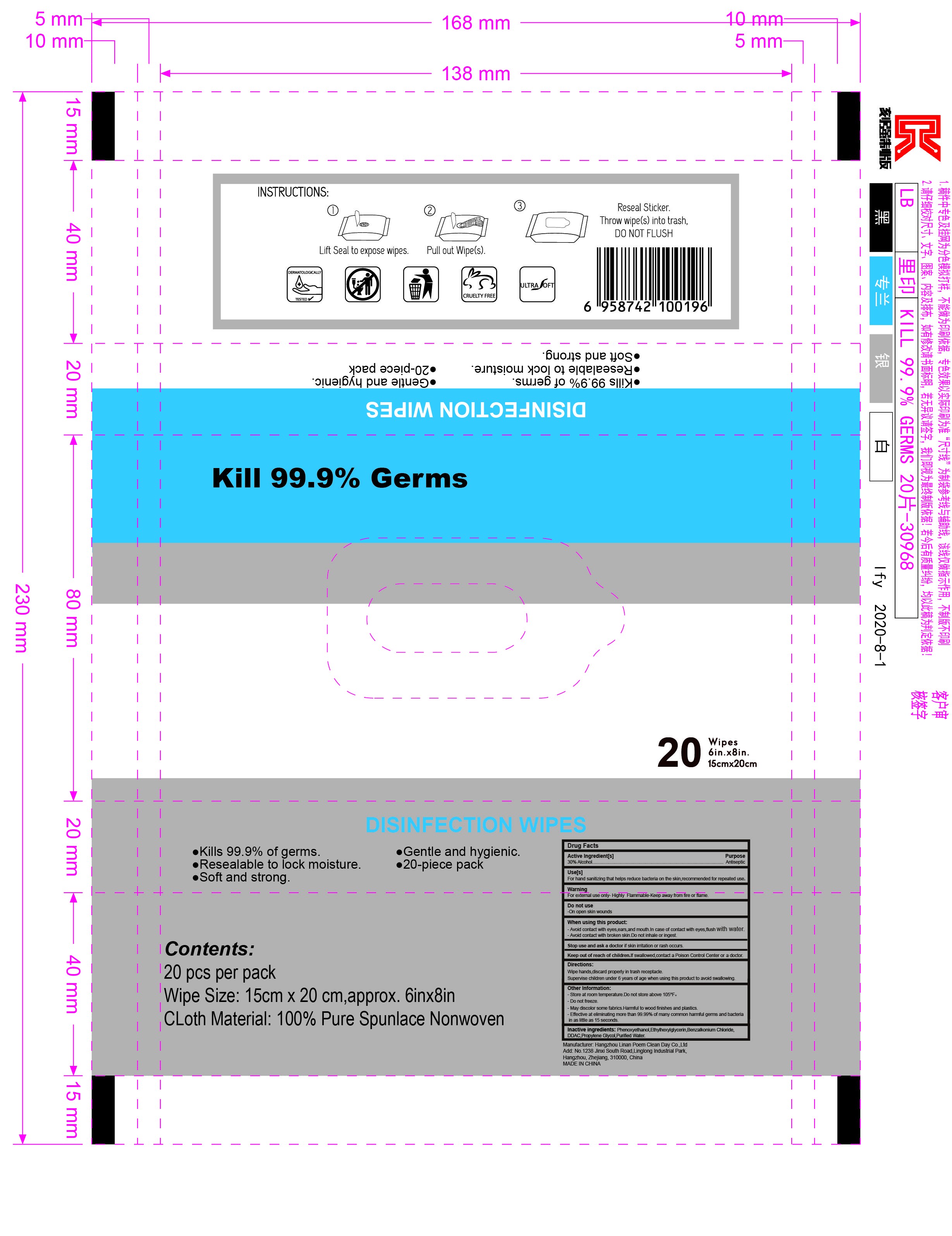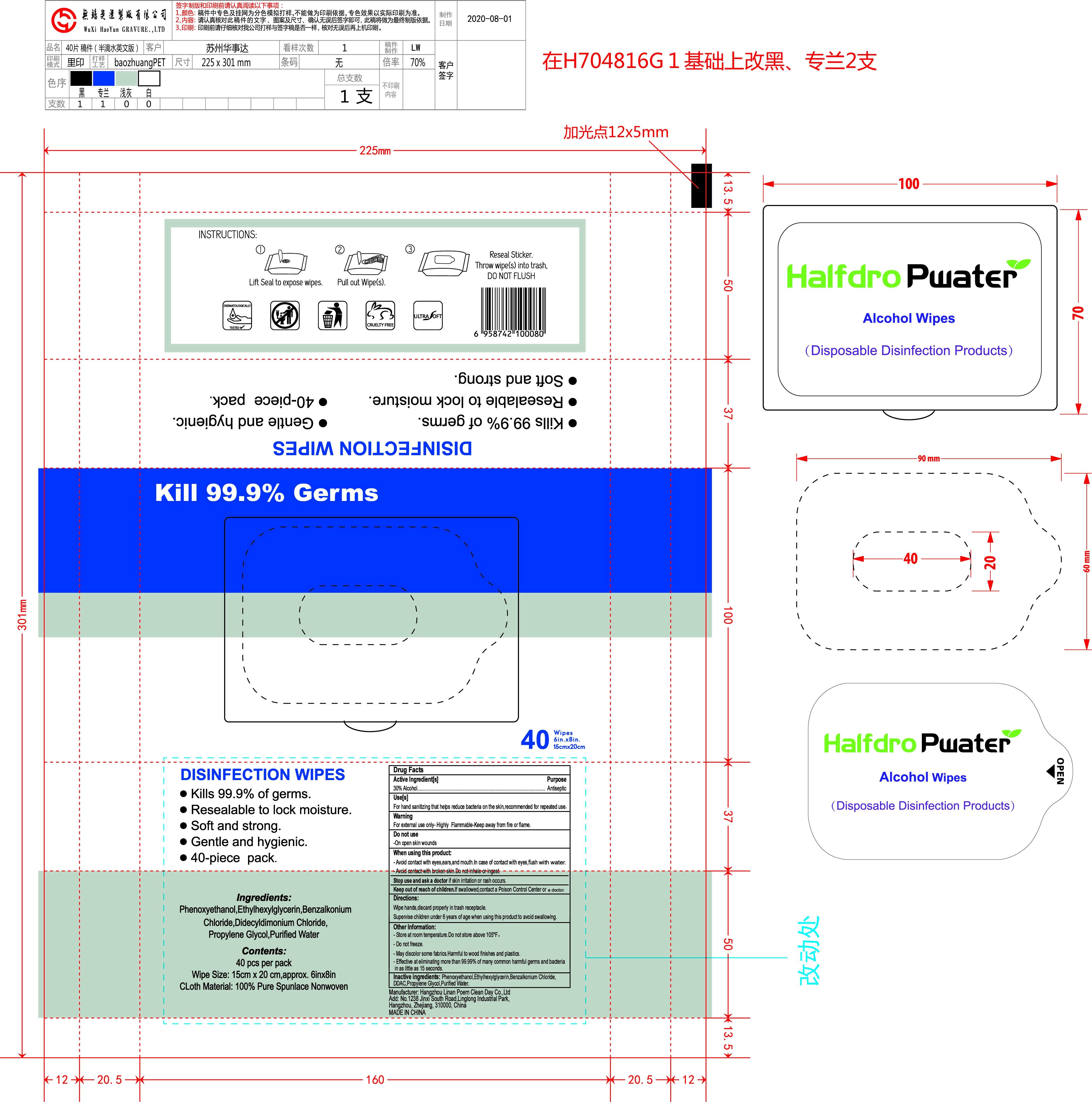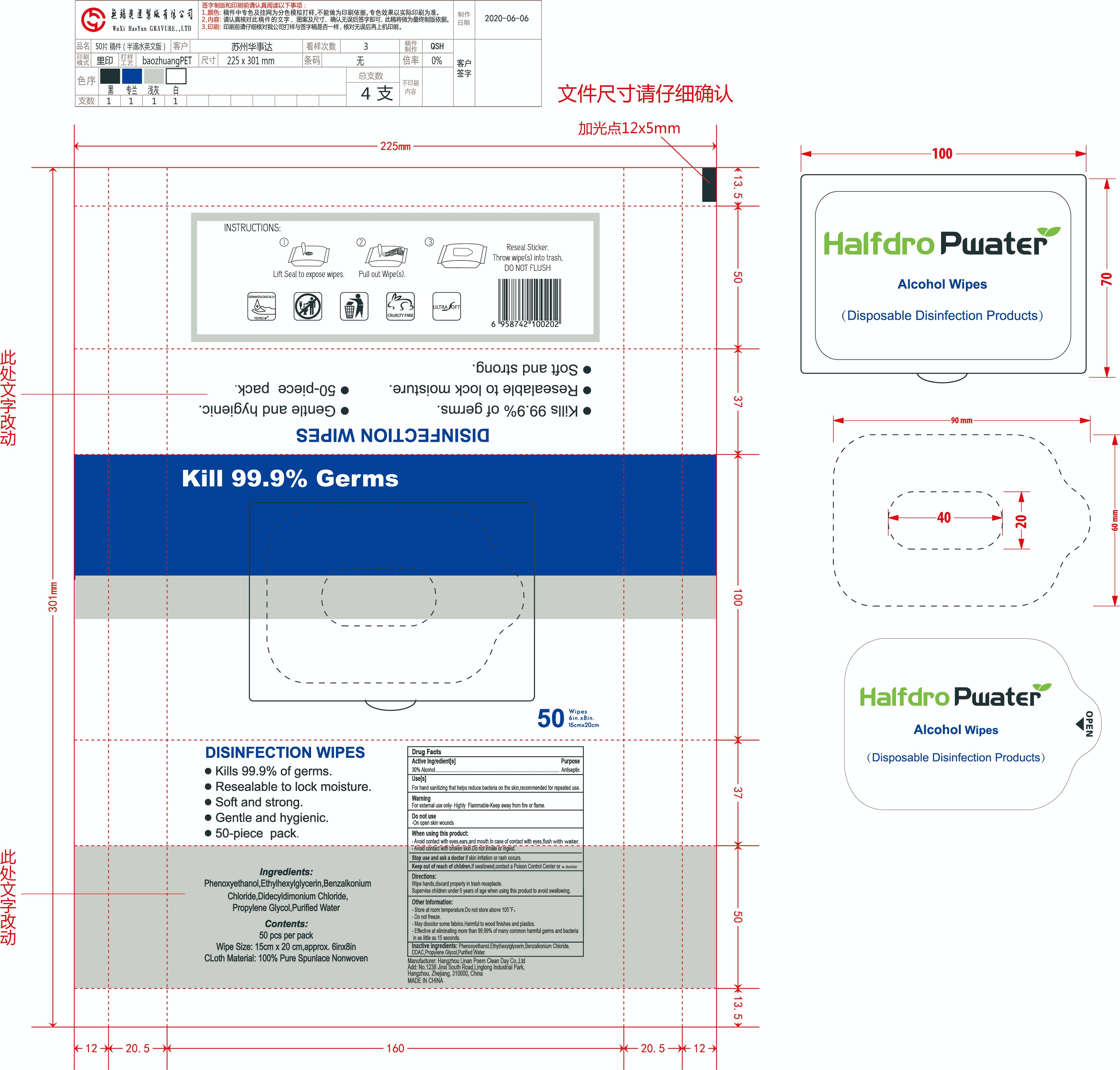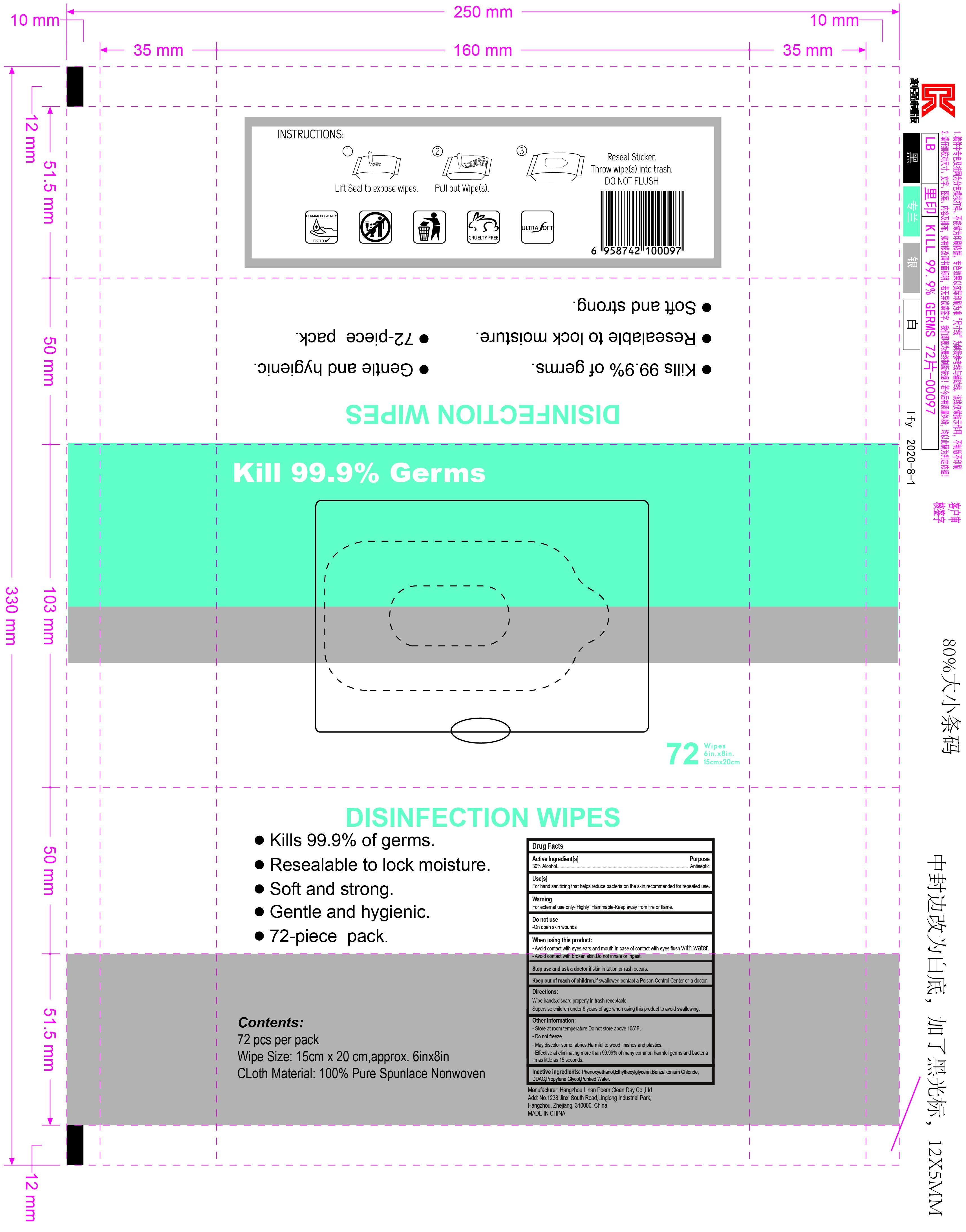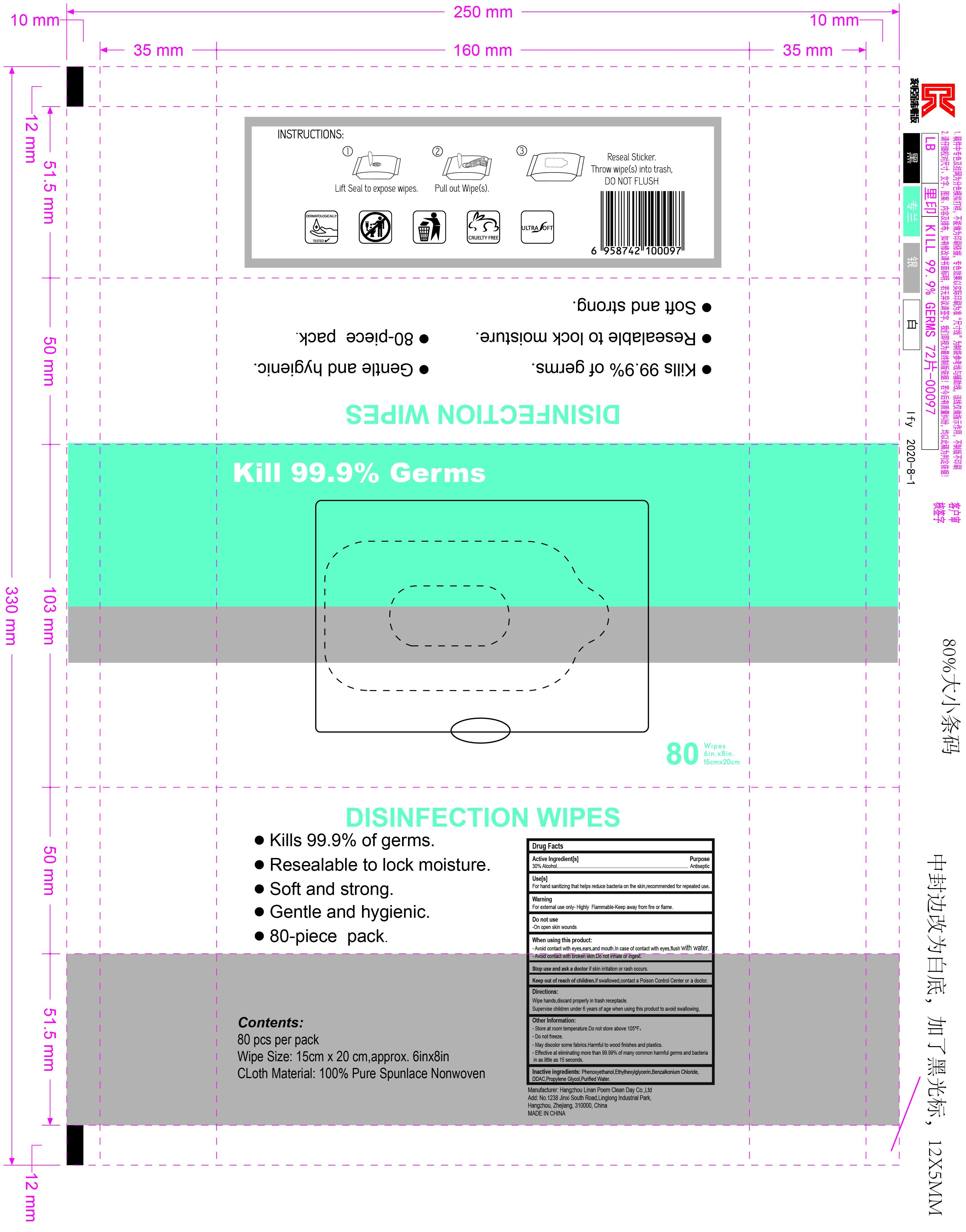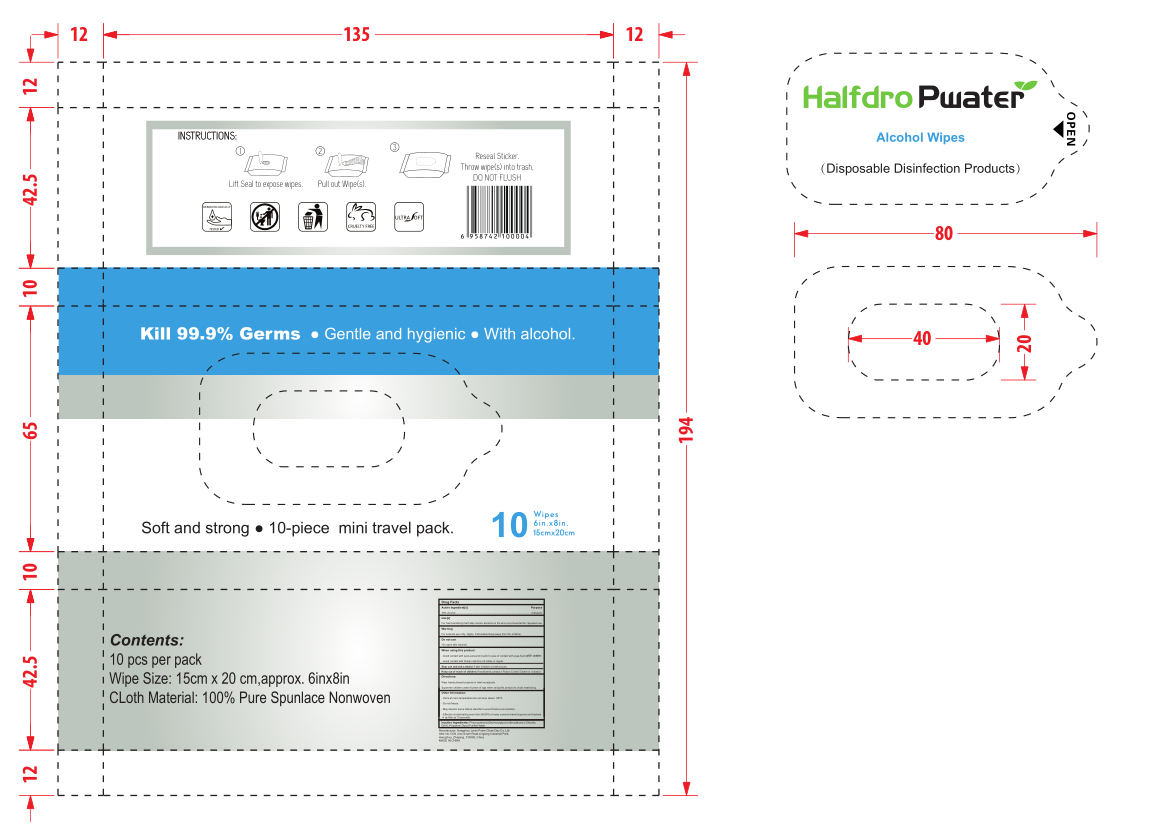 DRUG LABEL: Antibacterial Wet Wipes
NDC: 56076-004 | Form: CLOTH
Manufacturer: Hangzhou Linan Poem Clean Day Co., Ltd.
Category: otc | Type: HUMAN OTC DRUG LABEL
Date: 20200804

ACTIVE INGREDIENTS: ALCOHOL 14.175 g/10 1; BENZALKONIUM CHLORIDE 0.042 g/10 1; DIDECYLDIMONIUM CHLORIDE 0.0567 g/10 1
INACTIVE INGREDIENTS: WATER; ETHYLHEXYLGLYCERIN; PROPYLENE GLYCOL; PHENOXYETHANOL

DOSAGE AND ADMINISTRATION

keep away from heat source, store in a cool and dry place, and avoid direct sunlight.

INACTIVE INGREDIENT

Phenoxyethanol,Ethylhexylglycerin.Propylene Glycol.Purified Water

INDICATIONS AND USAGE

Open the adhesive, take out the wipes,Wipe back and forth.

ACTIVE INGREDIENT

Ethanol

Benzalkonium Chloride

Didecyldimonium Chloride

keep out of reach of children

PURPOSE

Disinfection
Sterilization
No Rinseing

WARNINGS

Please keep the wipes out of reach of children to avoid misuse. This is an insoluble product. Do not throw it into the toilet to avoid blockage.